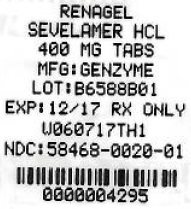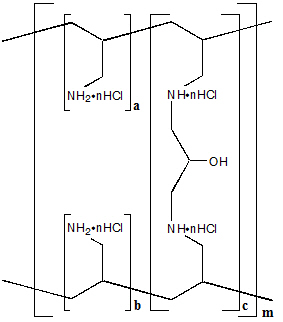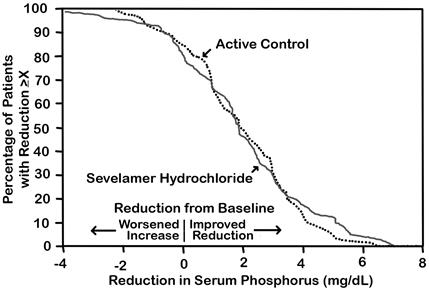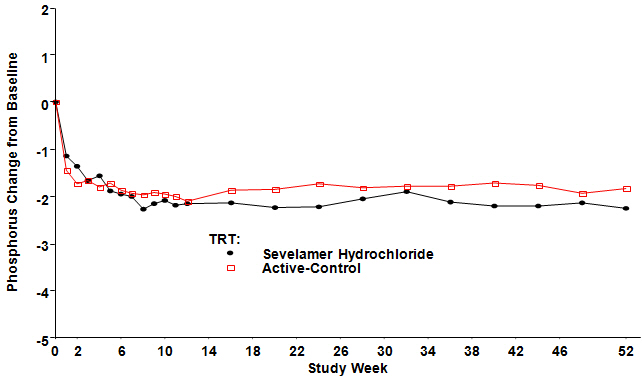 DRUG LABEL: RENAGEL
NDC: 68151-4295 | Form: TABLET
Manufacturer: Carilion Materials Management
Category: prescription | Type: HUMAN PRESCRIPTION DRUG LABEL
Date: 20180214

ACTIVE INGREDIENTS: SEVELAMER HYDROCHLORIDE 400 mg/1 1
INACTIVE INGREDIENTS: SILICON DIOXIDE 1.6 mg/1 1; STEARIC ACID 1.6 mg/1 1; WATER 32.3 mg/1 1; HYPROMELLOSE 2910 (5 MPA.S) 8.35 mg/1 1; HYPROMELLOSE 2910 (15 MPA.S) 8.35 mg/1 1; FERROSOFERRIC OXIDE; PROPYLENE GLYCOL; ISOPROPYL ALCOHOL

HIGHLIGHTS OF PRESCRIBING INFORMATION

These highlights do not include all the information needed to use Renagel safely and effectively. See full prescribing information for Renagel.
Renagel (sevelamer hydrochloride) Tablet for Oral use
Initial U.S. Approval: 2000

RECENT MAJOR CHANGES

Contraindications (4) | 03/2016

1 INDICATIONS AND USAGE

- Renagel® is a phosphate binder indicated for the control of serum phosphorus in patients with chronic kidney disease on dialysis. (1)

2 DOSAGE AND ADMINISTRATION

- Starting dose is one or two 800 mg or two to four 400 mg tablets three times per day with meals. (2)
- Adjust by one tablet per meal in two week intervals as needed to obtain serum phosphorus target (3.5 to 5.5 mg/dL). (2)

3 DOSAGE FORMS AND STRENGTHS

- Tablets: 800 mg and 400 mg (3)

4 CONTRAINDICATIONS

- Bowel obstruction. (4)
- Known hypersensitivity to sevelamer hydrochloride or to any of the excipients. (4)

5 WARNINGS AND PRECAUTIONS

- Serious cases of dysphagia, bowel obstruction, and perforation have been associated with sevelamer use, some requiring hospitalization and surgery. (5.1)

6 ADVERSE REACTIONS

- The most common reasons for discontinuing treatment were gastrointestinal adverse reactions. (6.1)
- In a parallel design study of 12 weeks duration, treatment-emergent adverse reactions to Renagel Tablets in peritoneal dialysis patients included dyspepsia (12%), peritonitis (8%), diarrhea (5%), nausea (5%), constipation (4%), pruritus (4%), abdominal distension (3%), vomiting (3%), fatigue (3%), anorexia (3%), and arthralgia (3%). (6.1)
- Similar reactions at similar rates occurred in hemodialysis and peritoneal dialysis patients. (6.1)
- Cases of fecal impaction and, less commonly, ileus, bowel obstruction, and bowel perforation have been reported. (6.2)

To report SUSPECTED ADVERSE REACTIONS, contact Genzyme Corporation at 1-800-847-0069 and or FDA at 1-800-FDA-1088 or www.fda.gov/medwatch.

7 DRUG INTERACTIONS

- When clinically significant drug interactions are expected, consider separation of the timing of administration and/or monitor clinical responses or blood levels of the concomitant medication. (7)
- Sevelamer did not alter the pharmacokinetics of digoxin, enalapril, iron, metoprolol, and warfarin. (7)
- Sevelamer has demonstrated interaction with ciprofloxacin, and mycophenolate mofetil, and therefore these drugs should be dosed separately from Renagel. (7)

FULL PRESCRIBING INFORMATION

1 INDICATIONS AND USAGE

RENAGEL® (sevelamer hydrochloride) is indicated for the control of serum phosphorus in patients with chronic kidney disease (CKD) on dialysis. The safety and efficacy of Renagel in CKD patients who are not on dialysis have not been studied.

2 DOSAGE AND ADMINISTRATION

Patients Not Taking a Phosphate Binder. The recommended starting dose of Renagel is 800 to 1600 mg, which can be administered as one or two 800 mg Renagel® Tablets, or two to four 400 mg Renagel® Tablets, with meals based on serum phosphorus level. Table 1 provides recommended starting doses of Renagel for patients not taking a phosphate binder.

Table 1: Starting Dose for Dialysis Patients Not Taking a Phosphate Binder
Serum Phosphorus | Renagel® 800 mg | Renagel® 400 mg
>5.5 and <7.5 mg/dL | 1 tablet three times daily with meals | 2 tablets three times daily with meals
≥7.5 and <9.0 mg/dL | 2 tablets three times daily with meals | 3 tablets three times daily with meals
≥9.0 mg/dL | 2 tablets three times daily with meals | 4 tablets three times daily with meals

Patients Switching from Calcium Acetate. In a study in 84 CKD patients on hemodialysis, a similar reduction in serum phosphorus was seen with equivalent doses (approximately mg for mg) of Renagel and calcium acetate. Table 2 gives recommended starting doses of Renagel based on a patient's current calcium acetate dose.

Table 2: Starting Dose for Dialysis Patients Switching From Calcium Acetate to Renagel
Calcium Acetate 667 mg (Tablets per meal) | Renagel® 800 mg (Tablets per meal) | Renagel® 400 mg (Tablets per meal)
1 tablet | 1 tablet | 2 tablets
2 tablets | 2 tablets | 3 tablets
3 tablets | 3 tablets | 5 tablets

Dose Titration for All Patients Taking Renagel. Dosage should be adjusted based on the serum phosphorus concentration with a goal of lowering serum phosphorus to 5.5 mg/dL or less. The dose may be increased or decreased by one tablet per meal at two-week intervals as necessary. Table 3 gives a dose titration guideline. The average dose in a Phase 3 trial designed to lower serum phosphorus to 5.0 mg/dL or less was approximately three Renagel 800 mg tablets per meal. The maximum average daily Renagel dose studied was 13 grams.

Table 3: Dose Titration Guideline
Serum Phosphorus | Renagel® Dose
>5.5 mg/dL | Increase 1 tablet per meal at 2 week intervals
3.5–5.5 mg/dL | Maintain current dose
<3.5 mg/dL | Decrease 1 tablet per meal

3 DOSAGE FORMS AND STRENGTHS

800 mg and 400 mg tablets.

4 CONTRAINDICATIONS

Renagel is contraindicated in patients with bowel obstruction.

Renagel is contraindicated in patients with known hypersensitivity to sevelamer hydrochloride or to any of the excipients.

5 WARNINGS AND PRECAUTIONS

5.1 Gastrointestinal Adverse Events

Cases of dysphagia and esophageal tablet retention have been reported in association with use of the tablet formulation of sevelamer, some requiring hospitalization and intervention. Consider using sevelamer suspension in patients with a history of swallowing disorders.

Cases of bowel obstruction and perforation have also been reported with sevelamer use.

Patients with dysphagia, swallowing disorders, severe gastrointestinal (GI) motility disorders including severe constipation, or major GI tract surgery were not included in the Renagel clinical studies.

5.2 Monitor Serum Chemistries

Bicarbonate and chloride levels should be monitored.

5.3 Monitor for Reduced Vitamins D, E, K (clotting factors) and Folic Acid Levels

In preclinical studies in rats and dogs, sevelamer hydrochloride reduced vitamins D, E, and K (coagulation parameters) and folic acid levels at doses of 6 to 10 times the recommended human dose. In short-term clinical trials, there was no evidence of reduction in serum levels of vitamins. However, in a one-year clinical trial, 25-hydroxyvitamin D (normal range 10 to 55 ng/mL) fell from 39 ± 22 ng/mL to 34 ± 22 ng/mL (p<0.01) with sevelamer hydrochloride treatment. Most (approximately 75%) patients in sevelamer hydrochloride clinical trials received vitamin supplements, which is typical of patients on dialysis.

6 ADVERSE REACTIONS

6.1 Clinical Trials Experience

Because clinical trials are conducted under widely varying conditions, adverse reaction rates observed in the clinical trials of a drug can not be directly compared to rates in the clinical trials of another drug and may not reflect the rates observed in practice.

In a parallel design study of sevelamer hydrochloride with treatment duration of 52 weeks, adverse reactions reported for sevelamer hydrochloride (n=99) were similar to those reported for the active-control group (n=101). Overall adverse reactions among those treated with sevelamer hydrochloride occurring in >5% of patients included: vomiting (22%), nausea (20%), diarrhea (19%), dyspepsia (16%), abdominal pain (9%), flatulence (8%), and constipation (8%). A total of 27 patients treated with sevelamer and 10 patients treated with comparator withdrew from the study due to adverse reactions.

Based on studies of 8 to 52 weeks, the most common reason for withdrawal from Renagel was gastrointestinal adverse reactions (3%–16%).

In 143peritoneal dialysis patients studied for 12 weeks, most adverse reactions were similar to adverse reactions observed in hemodialysis patients. The most frequently occurring treatment-emergent serious adverse reaction was peritonitis (8 reactions in 8 patients [8%] in the sevelamer group and 2 reactions in 2 patients [4%] on active control). Thirteen patients (14%) in the sevelamer group and 9 patients (20%) in the active-control group discontinued, mostly for gastrointestinal adverse reactions. Patients on peritoneal dialysis should be closely monitored to ensure the reliable use of appropriate aseptic technique with the prompt recognition and management of any signs and symptoms associated with peritonitis.

6.2 Postmarketing Experience

The following adverse reactions have been identified during postapproval use of sevelamer hydrochloride (Renagel®): hypersensitivity, pruritus, rash, abdominal pain, fecal impaction and uncommon cases of ileus, intestinal obstruction, and intestinal perforation. Appropriate medical management should be given to patients who develop constipation or have worsening of existing constipation to avoid severe complications.

Because these reactions are reported voluntarily from a population of uncertain size, it is not always possible to estimate their frequency or to establish a causal relationship to drug exposure.

7 DRUG INTERACTIONS

There are no empirical data on avoiding drug interactions between Renagel® and most concomitant oral drugs. For oral medication where a reduction in the bioavailability of that medication would have a clinically significant effect on its safety or efficacy (e.g., cyclosporine, tacrolimus, levothyroxine), consider separation of the timing of the administration of the two drugs [see Clinical Pharmacology (12.3)]. The duration of separation depends upon the absorption characteristics of the medication concomitantly administered, such as the time to reach peak systemic levels and whether the drug is an immediate-release or an extended-release product. Where possible consider monitoring clinical responses and/or blood levels of concomitant drugs that have a narrow therapeutic range.

Table 4: Sevelamer Drug Interactions
Oral drugs for which sevelamer did not alter the pharmacokinetics when administered concomitantly
Digoxin
Enalapril
Iron
Metoprolol
Warfarin
Oral drugs that have demonstrated interaction with sevelamer and are to be dosed separately from Renagel
 | Dosing Recommendations
Ciprofloxacin | Take at least 2 hours before or 6 hours after sevelamer
Mycophenolate mofetil | Take at least 2 hours before sevelamer

8 USE IN SPECIFIC POPULATIONS

8.1 Pregnancy

TERATOGENIC EFFECTS

Pregnancy Category C: The effect of Renagel on the absorption of vitamins and other nutrients has not been studied in pregnant women. Requirements for vitamins and other nutrients are increased in pregnancy. In pregnant rats given doses of Renagel during organogenesis, reduced or irregular ossification of fetal bones, probably due to a reduced absorption of fat-soluble vitamin D, occurred. In pregnant rabbits given oral doses of Renagel by gavage during organogenesis, an increase of early resorptions occurred [see Nonclinical Toxicology (13.1)].

8.2 Labor and Delivery

No Renagel treatment-related effects on labor and delivery were seen in animal studies. The effects of Renagel on labor and delivery in humans are not known [see Nonclinical Toxicology (13.1)].

8.4 Pediatric Use

The safety and efficacy of Renagel has not been established in pediatric patients.

8.5 Geriatric Use

Clinical studies of Renagel did not include sufficient numbers of subjects aged 65 and over to determine whether they respond differently from younger subjects. Other reported clinical experience has not identified differences in responses between the elderly and younger patients. In general, dose selection for an elderly patient should be cautious, usually starting at the low end of the dosing range.

10 OVERDOSAGE

Renagel has been given to normal healthy volunteers in doses of up to 14 grams per day for eight days with no adverse effects. Renagel has been given in average doses up to 13 grams per day to hemodialysis patients. There are no reports of overdosage with Renagel in patients. Since Renagel is not absorbed, the risk of systemic toxicity is low.

11 DESCRIPTION

The active ingredient in Renagel Tablets is sevelamer hydrochloride, a polymeric amine that binds phosphate and is meant for oral administration. Sevelamer hydrochloride is poly(allylamine hydrochloride) crosslinked with epichlorohydrin in which 40% of the amines are protonated. It is known chemically as poly(allylamine-co-N,N'-diallyl-1,3-diamino-2-hydroxypropane) hydrochloride. Sevelamer hydrochloride is hydrophilic, but insoluble in water. The structure is represented in Figure 1.

Figure 1: Chemical Structure of Sevelamer Hydrochloride

 | a, b = number of primary amine groups | a + b = 9
 | c = number of crosslinking groups | c = 1
 | n = fraction of protonated amines | n = 0.4
 | m = large number to indicate extended polymer network

The primary amine groups shown in the structure are derived directly from poly(allylamine hydrochloride). The crosslinking groups consist of two secondary amine groups derived from poly(allylamine hydrochloride) and one molecule of epichlorohydrin.

Renagel® Tablets: Each film-coated tablet of Renagel contains either 800 mg or 400 mg of sevelamer hydrochloride on an anhydrous basis. The inactive ingredients are hypromellose, diacetylated monoglyceride, colloidal silicon dioxide, and stearic acid. The tablet imprint contains iron oxide black ink.

12 CLINICAL PHARMACOLOGY

Patients with chronic kidney disease (CKD) on dialysis retain phosphorus and can develop hyperphosphatemia. High serum phosphorus can precipitate serum calcium resulting in ectopic calcification. When the product of serum calcium and phosphorus concentrations (Ca × P) exceeds 55 mg^2/dL^2, there is an increased risk that ectopic calcification will occur. Hyperphosphatemia plays a role in the development of secondary hyperparathyroidism in renal insufficiency.

Treatment of hyperphosphatemia includes reduction in dietary intake of phosphate, inhibition of intestinal phosphate absorption with phosphate binders, and removal of phosphate with dialysis. Renagel taken with meals has been shown to decrease serum phosphorus concentrations in patients with CKD who are on dialysis.

12.1 Mechanism of Action

Renagel contains sevelamer hydrochloride, a non-absorbed binding crosslinked polymer. It contains multiple amines separated by one carbon from the polymer backbone. These amines exist in a protonated form in the intestine and interact with phosphate molecules through ionic and hydrogen bonding. By binding phosphate in the dietary tract and decreasing absorption, sevelamer hydrochloride lowers the phosphate concentration in the serum.

12.2 Pharmacodynamics

In addition to effects on serum phosphate levels, sevelamer hydrochloride has been shown to bind bile acids in vitro and in vivo in experimental animal models. Bile acid binding by ion exchange resins is a well-established method of lowering blood cholesterol. Because sevelamer binds bile acids, it may interfere with normal fat absorption and thus may reduce absorption of fat-soluble vitamins such as A, D, and K. In clinical trials of sevelamer hydrochloride, both the mean total and LDL cholesterol declined by 15% to 31%. This effect is observed after 2 weeks. Triglycerides, HDL cholesterol, and albumin did not change.

12.3 Pharmacokinetics

A mass balance study using ^14C-sevelamer hydrochloride in 16 healthy male and female volunteers showed that sevelamer hydrochloride is not systemically absorbed. No absorption studies have been performed in patients with renal disease.

Drug Interactions

In vivo

Sevelamer carbonate has been studied in human drug-drug interaction studies (9.6 grams once daily with a meal) with warfarin and digoxin. Sevelamer hydrochloride, which contains the same active moiety as sevelamer carbonate, has been studied in human drug-drug interaction studies (2.4–2.8 grams single dose or three times daily with meals or two times daily without meals) with ciprofloxacin, digoxin, enalapril, iron, metoprolol, mycophenolate mofetil and warfarin.

Coadministered single dose of 2.8 grams of sevelamer hydrochloride in fasted state decreased the bioavailability of ciprofloxacin by approximately 50% in healthy subjects.

Concomitant administration of sevelamer and mycophenolate mofetil in adult and pediatric patients decreased the mean MPA Cmax and AUC0–12h by 36% and 26%, respectively.

Sevelamer carbonate or sevelamer hydrochloride did not alter the pharmacokinetics of a single dose of enalapril, digoxin, iron, metoprolol and warfarin when coadministered.

During postmarketing experience, cases of increased thyroid stimulating hormone (TSH) levels have been reported in patients coadministered sevelamer hydrochloride and levothyroxine. Reduction in concentrations of cyclosporine and tacrolimus leading to dose increases has also been reported in transplant patients when coadministered with sevelamer hydrochloride without any clinical consequences (e.g., graft rejection). The possibility of an interaction cannot be excluded with these drugs.

13 NONCLINICAL TOXICOLOGY

13.1 Carcinogenesis, Mutagenesis, Impairment of Fertility

Standard lifetime carcinogenicity bioassays were conducted in mice and rats. Rats were given sevelamer hydrochloride by diet at 0.3, 1, or 3 g/kg/day. There was an increased incidence of urinary bladder transitional cell papilloma in male rats of the high-dose group (human equivalent dose twice the maximum clinical trial dose of 13 g). Mice received dietary administration of sevelamer hydrochloride at doses of up to 9 g/kg/day (human equivalent dose 3 times the maximum clinical trial dose). There was no increased incidence of tumors observed in mice.

In an in vitro mammalian cytogenetic test with metabolic activation, sevelamer hydrochloride caused a statistically significant increase in the number of structural chromosome aberrations. Sevelamer hydrochloride was not mutagenic in the Ames bacterial mutation assay.

Sevelamer hydrochloride did not impair the fertility of male or female rats in a dietary administration study in which the females were treated from 14 days prior to mating through gestation and the males were treated for 28 days prior to mating. The highest dose in this study was 4.5 g/kg/day (human equivalent dose 3 times the maximum clinical trial dose of 13 g).

In pregnant rats given dietary doses of 0.5, 1.5 or 4.5 g/kg/day of sevelamer hydrochloride during organogenesis, reduced or irregular ossification of fetal bones, probably due to a reduced absorption of fat-soluble vitamin D, occurred in mid and high-dose groups (human equivalent doses less than the maximum clinical trial dose of 13 g). In pregnant rabbits given oral doses of 100, 500, or 1000 mg/kg/day of sevelamer hydrochloride by gavage during organogenesis, an increase of early resorptions occurred in the high-dose group (human equivalent dose twice the maximum clinical trial dose).

14 CLINICAL STUDIES

The ability of Renagel to lower serum phosphorus in CKD patients on dialysis was demonstrated in six clinical trials: one double-blind placebo-controlled 2-week study (Renagel N=24); two open-label uncontrolled 8-week studies (Renagel N=220) and three active-controlled open-label studies with treatment durations of 8 to 52 weeks (Renagel N=256). Three of the active-controlled studies are described here. One is a crossover study with two 8-week periods comparing Renagel to an active control. The second is a 52-week parallel study comparing Renagel with active control. The third is a 12-week parallel study comparing Renagel and active control in peritoneal dialysis patients.

14.1 Active-Control, Cross-Over Study in Hemodialysis Patients

Eighty-four CKD patients on hemodialysis who were hyperphosphatemic (serum phosphorus >6.0 mg/dL) following a two-week phosphate-binder washout period received Renagel and active control for eight weeks each in random order. Treatment periods were separated by a two-week phosphate-binder washout period. Patients started on treatment three times per day with meals. Over each eight-week treatment period, at three separate time points the dose of Renagel could be titrated up 1 capsule or tablet per meal (3 per day) to control serum phosphorus, the dose of active control could also be altered to attain phosphate control. Both treatments significantly decreased mean serum phosphorus by about 2 mg/dL (Table 5).

Table 5: Mean Serum Phosphorus (mg/dL) at Baseline and Endpoint
 | Renagel® (N=81) | Active-Control (N=83)
Baseline at End of Washout | 8.4 | 8.0
Endpoint | 6.4 | 5.9
Change from Baseline at Endpoint (95% Confidence Interval) | -2.0 [p<0.0001, within treatment group comparison] (-2.5, -1.5) | -2.1 (-2.6, -1.7)

The distribution of responses is shown in Figure 2. The distributions are similar for sevelamer hydrochloride and active control. The median response is a reduction of about 2 mg/dL in both groups. About 50% of subjects have reductions between 1 and 3 mg/dL.

Figure 2: Percentage of Patients (Y-axis) Attaining a Phosphorus Reduction from Baseline (mg/dL) at Least as Great as the Value of the X-axis.

Average daily Renagel dose at the end of treatment was 4.9 g (range of 0.0 to 12.6 g).

14.2 Active-Control, Parallel Study in Hemodialysis Patients

Two hundred CKD patients on hemodialysis who were hyperphosphatemic (serum phosphorus >5.5 mg/dL) following a two-week phosphate-binder washout period were randomized to receive Renagel 800 mg tablets (N=99) or an active control (N=101). The two treatments produced similar decreases in serum phosphorus. At week 52, using last observation carried forward, Renagel and active control both significantly decreased mean serum phosphorus (Table 6).

Table 6: Mean Serum Phosphorus (mg/dL) and Ion Product at Baseline and Change from Baseline to End of Treatment
 | Renagel® (N=94) | Active-Control (N=98)
Phosphorus
Baseline | 7.5 | 7.3
Change from Baseline at Endpoint | -2.1 | -1.8
Ca × Phosphorus Ion Product
Baseline | 70.5 | 68.4
Change from Baseline at Endpoint | -19.4 | -14.2

Sixty-one percent of Renagel patients and 73% of the control patients completed the full 52 weeks of treatment.

Figure 3, a plot of the phosphorus change from baseline for the completers, illustrates the durability of response for patients who are able to remain on treatment.

Figure 3: Mean Phosphorus Change from Baseline for Patients who Completed 52 Weeks of Treatment

Average daily Renagel dose at the end of treatment was 6.5 g (range of 0.8 to 13 g).

14.3 Active-Control, Parallel Study in Peritoneal Dialysis Patients

One hundred and forty-three patients on peritoneal dialysis, who were hyperphosphatemic (serum phosphorus >5.5 mg/dL) following a two-week phosphate-binder washout period, were randomized to receive Renagel® (N=97) or active control (N=46) open label for 12 weeks. Average daily Renagel dose at the end of treatment was 5.9 g (range 0.8 to 14.3 g). There were statistically significant changes in serum phosphorus (p<0.001) for Renagel (-1.6 mg/dL from baseline of 7.5 mg/dL), similar to the active control.

16 HOW SUPPLIED/STORAGE AND HANDLING

Product: 68151-4295

NDC: 68151-4295-1 1 TABLET in a BLISTER PACK

17 PATIENT COUNSELING INFORMATION

Dosing Recommendations

The prescriber should inform patients to take Renagel with meals and adhere to their prescribed diets. Instructions should be given on concomitant medications that should be dosed apart from Renagel.

Adverse Reactions

Renagel may cause constipation that if left untreated may lead to severe complications. Patients should be cautioned to report new onset or worsening of existing constipation promptly to their physician.

Manufactured By:

Genzyme Ireland Ltd.

For: Genzyme Corporation

500 Kendall Street

Cambridge, MA 02142 USA